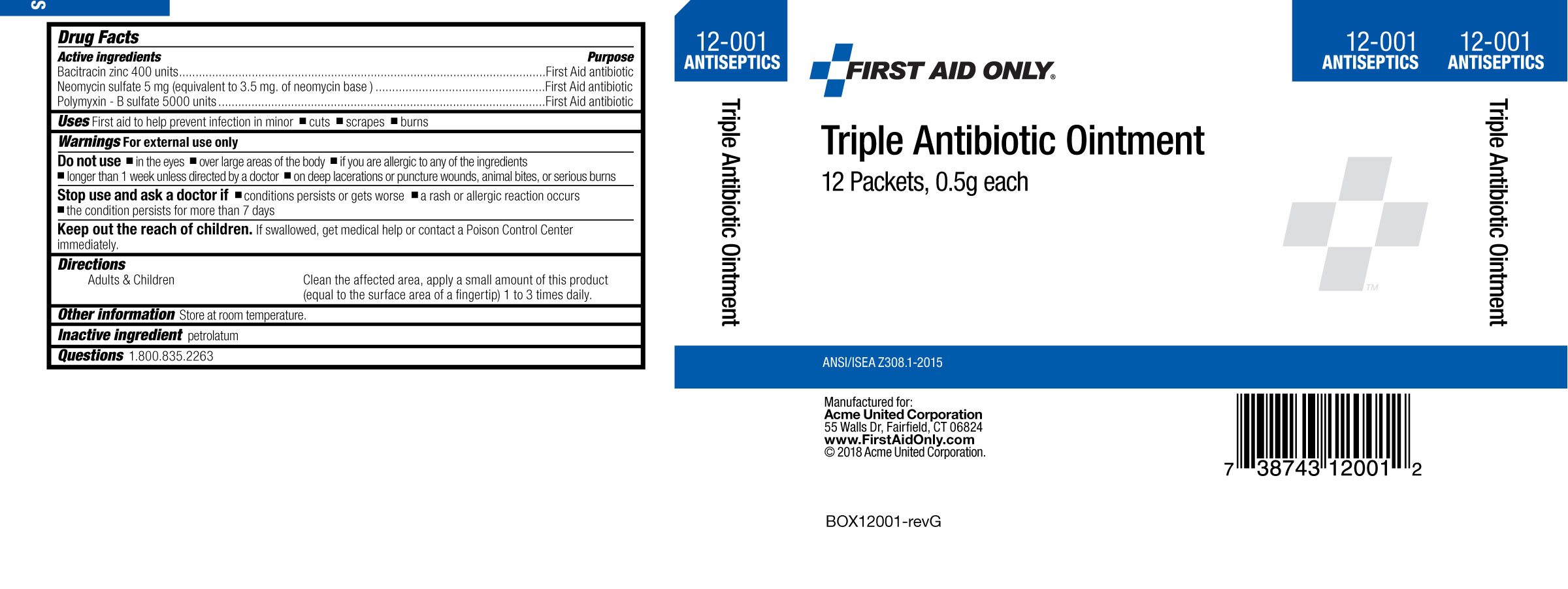 DRUG LABEL: First Aid Only Triple Antibiotic
NDC: 0924-5605 | Form: OINTMENT
Manufacturer: Acme united Corporation
Category: otc | Type: HUMAN OTC DRUG LABEL
Date: 20191112

ACTIVE INGREDIENTS: BACITRACIN ZINC 417.8 [iU]/1 g; POLYMYXIN B SULFATE 5322.8 [iU]/1 g; NEOMYCIN SULFATE 3.5 mg/1 g
INACTIVE INGREDIENTS: PETROLATUM

First Aid Only Triple Antibiotic Ointment

Active ingredients

Bacitracin zinc 400 units

Neomycin sulfate (5 mg equivalent to 3.5 mg Neomycin base)

Polymyxin B sulfate 5000 units

Purpose

First aid antibiotic

First aid antibiotic

First aid antibiotic

Uses

First aid to help prevent infection in minor •cuts •scrapes •burns

Warnings

For external use only

Do not use

- in the eyes • over large areas of the body •if you are allergic to any of the ingredients •longer than 1 week unless directed by a doctor •on deep lacerations or puncture wounds, animal bites, or serious burns

Stop use and ask a doctor if •condition persists or gets worse, •a rash or allergic reaction occurs, •the condition persists for more than 7 days

KEEP OUT OF REACH OF CHILDREN

Keep out of the reach of children. If swallowed, get medical help or contact a Poison Control Center immediately.

DOSAGE AND ADMINISTRATION

Adults and Children Clean the affected area, apply a small amount of this product

(equal to the surface area of a fingertip) 1 to 3 times daily.

Other information

Store at room temperature.

Inactive ingredient

petrolatum

Questions or comments?

Questions 1.800.835.2263

Principal Display Panel

Carton Image